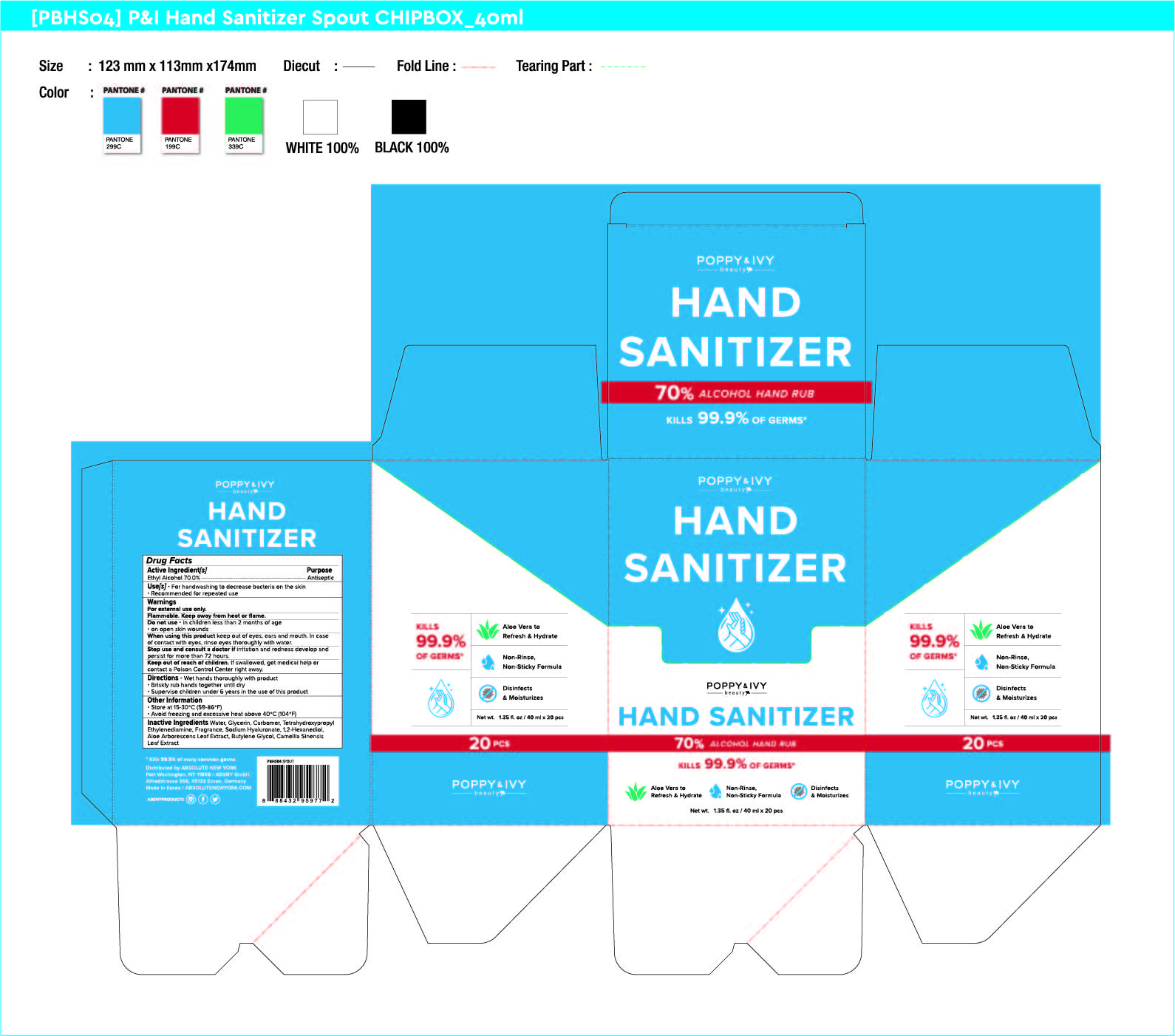 DRUG LABEL: POPPY and IVY HAND SANITIZER
NDC: 74004-147 | Form: GEL
Manufacturer: Ester Co., Ltd.
Category: otc | Type: HUMAN OTC DRUG LABEL
Date: 20200417

ACTIVE INGREDIENTS: ALCOHOL 28 g/40 mL
INACTIVE INGREDIENTS: ALOE ARBORESCENS LEAF; GREEN TEA LEAF; GLYCERIN; EDETOL; BUTYLENE GLYCOL; HYALURONATE SODIUM; CARBOMER HOMOPOLYMER, UNSPECIFIED TYPE; WATER; 1,2-HEXANEDIOL

[Ester Co., Ltd.-POPPY and IVY HAND SANITIZER] 40 ml X 20 : 74004-147-20